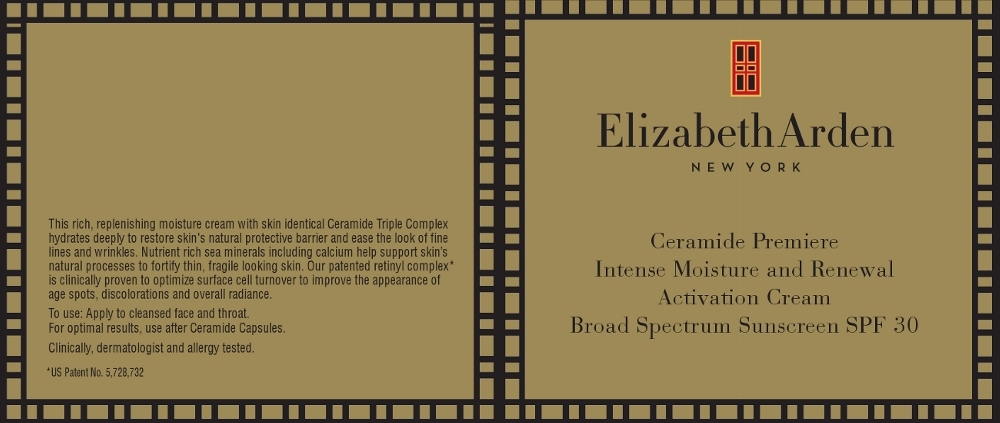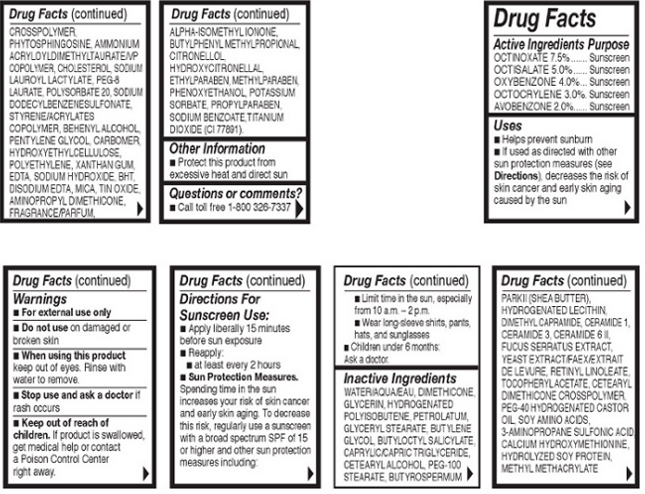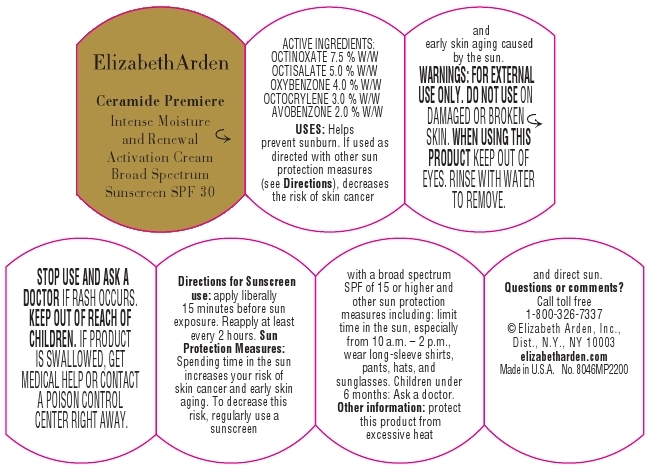 DRUG LABEL: Ceramide Premier Intense Moisture and Renewal Activation Broad Spectrum SPF 30
NDC: 67938-1145 | Form: CREAM
Manufacturer: Elizabeth Arden, Inc
Category: otc | Type: HUMAN OTC DRUG LABEL
Date: 20130430

ACTIVE INGREDIENTS: OCTINOXATE 3.68 g/49 g; OCTISALATE 2.45 g/49 g; OXYBENZONE 1.96 g/49 g; OCTOCRYLENE 1.47 g/49 g; AVOBENZONE 0.98 g/49 g
INACTIVE INGREDIENTS: WATER; DIMETHICONE; GLYCERIN; PETROLATUM; BUTYLENE GLYCOL; BUTYLOCTYL SALICYLATE; MEDIUM-CHAIN TRIGLYCERIDES; CETOSTEARYL ALCOHOL; PEG-100 STEARATE; SHEA BUTTER; HYDROGENATED SOYBEAN LECITHIN; DIMETHYL CAPRAMIDE; CERAMIDE 1; CERAMIDE 3; CERAMIDE 6 II; FUCUS SERRATUS; YEAST; RETINYL LINOLEATE; .ALPHA.-TOCOPHEROL ACETATE; POLYOXYL 40 HYDROGENATED CASTOR OIL; TRAMIPROSATE; PHYTOSPHINGOSINE; AMMONIUM ACRYLOYLDIMETHYLTAURATE/VP COPOLYMER; CHOLESTEROL; SODIUM LAUROYL LACTYLATE; PEG-8 LAURATE; POLYSORBATE 20; SODIUM DODECYLBENZENESULFONATE; DOCOSANOL; PENTYLENE GLYCOL; HIGH DENSITY POLYETHYLENE; XANTHAN GUM; EDETIC ACID; SODIUM HYDROXIDE; BUTYLATED HYDROXYTOLUENE; EDETATE DISODIUM; MICA; STANNIC OXIDE; ISOMETHYL-.ALPHA.-IONONE; BUTYLPHENYL METHYLPROPIONAL; HYDROXYCITRONELLAL; ETHYLPARABEN; METHYLPARABEN; PHENOXYETHANOL; POTASSIUM SORBATE; PROPYLPARABEN; SODIUM BENZOATE; TITANIUM DIOXIDE

BC1145

DESCRIPTION

This rich, replenishing moisture cream with skin identical Ceramide Triple Complex hydrates deeply to restore skin's natural protective barrier and ease the look of fine lines and wrinkles. Nutrient rich sea minerals including calcium help support skin’s natural processes to fortify thin, fragile looking skin. Our patented retinyl complex is clinically proven to optimize surface cell turnover to improve the appearance of age spots, discolorations and overall radiance.

DOSAGE AND ADMINISTRATION

To Use: Apply to cleansed face and throat.

Directions For Sunscreen Use:Apply liberally 15 minutes before sun exposure. Reapply at least every 2 hours.

Sun Protection Measures:Spending time in the sun increases your risk of skin cancer and early skin aging. To decrease mthis risk, regularly use a sunscreen with a broad spectrum SPF of 15 or higher and other sun protection measures including: Limit time in the sun, especially from 10 a.m. – 2 p.m. Wear long-sleeve shirts, pants, hats, and sunglasses

Children under 6 months: Ask a doctor.

OTC - ACTIVE INGREDIENT

Active Ingredients: Octinoxate 7.5%, Octisalate 5.0%, Oxybenzone 4.0%, Octocrylene 3.0%, Avobenzone 2.0%.

INACTIVE INGREDIENT

Inactive Ingredients: Water/Aqua/Eau, Dimethicone, Glycerin, Hydrogenated Polyisobutene, Petrolatum, Glyceryl Stearate, Butylene Glycol, Butyloctly Salicylate, Caprylic/Capric Triglyceride, Cetearyl Alochol, PEG-100 Stearate, Butyrospermum Parkii (Shea Butter), Hydrogenated Lecithin, Dimethylcapramide, Ceramide 1, Ceramide 3, Ceramide 6 II, Fucus Serratus Extract, Yeast Extract/Faex/Extrait de Levure, Retinyl Lonoleate, Tocopheryl Acetate, Cetearyl Dimethicone Crosspolymer, PEG-40 Hydrogenated Castor Oil, Soy Amino Acids, 3-Aminopropane Sulfonic Acid, Calcium Hydroxymethionine, Hydrolyzed Soy Protein, Methyl Methacrylate Crosspolymer, Phytosphingosine, Ammonium Acryloyldimethyltaurate/VP Copolymer, Cholesterol, Sodium Lauroyl Lactylate, PEG-8 Laurate, Polysorbate 20, Sodium Dodecylbenzenesulfonate, Styrene/Acrylates Copolymer, Behenyl Alcohol, Pentylene Glycol, Carbomer, Hydroxyethylcellulose, Polyethylene, Xanthan Gum, EDTA, Sodium Hydroxide, BHT, Disodium EDTA, Mica, Tin Oxide, Aminopropyl Dimethicone, Fragrance/Parfum, Alpha-Isomethyl Ionone, Butylpheyl Methylpropional, Citronellol, Hydroxycitronellal, Ethylparaben, Methylparaben, Phenoxyethanol, Potassium Sorbate, Propylparaben, Sodium Benzoate, Titanium Dioxide (CI 77891).

INDICATIONS AND USAGE

Apply to face and throat.

OTC - KEEP OUT OF REACH OF CHILDREN

Keep out of reach of children. If product is swallowed, get medical help or contact a Poison Control Center right away.

OTC - PURPOSE

Provides SPF 30 Sun Protection.

OTC - WHEN USING

Keep out of eyes.

WARNINGS

For external use only.

Do not use on damaged or broken skin.

When using this product keep out of eyes. Rinse with water to remove.

Stop use and ask a doctor if rash occurs.